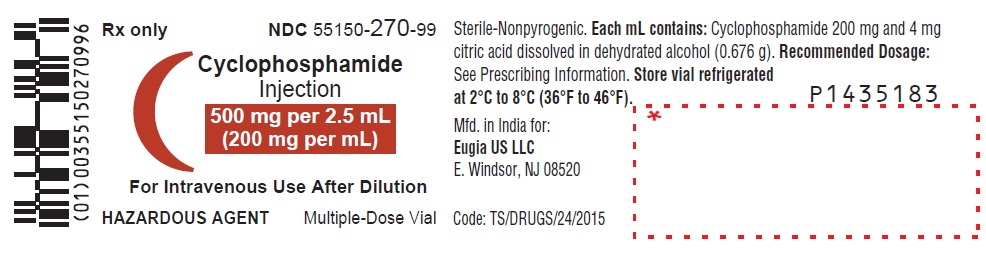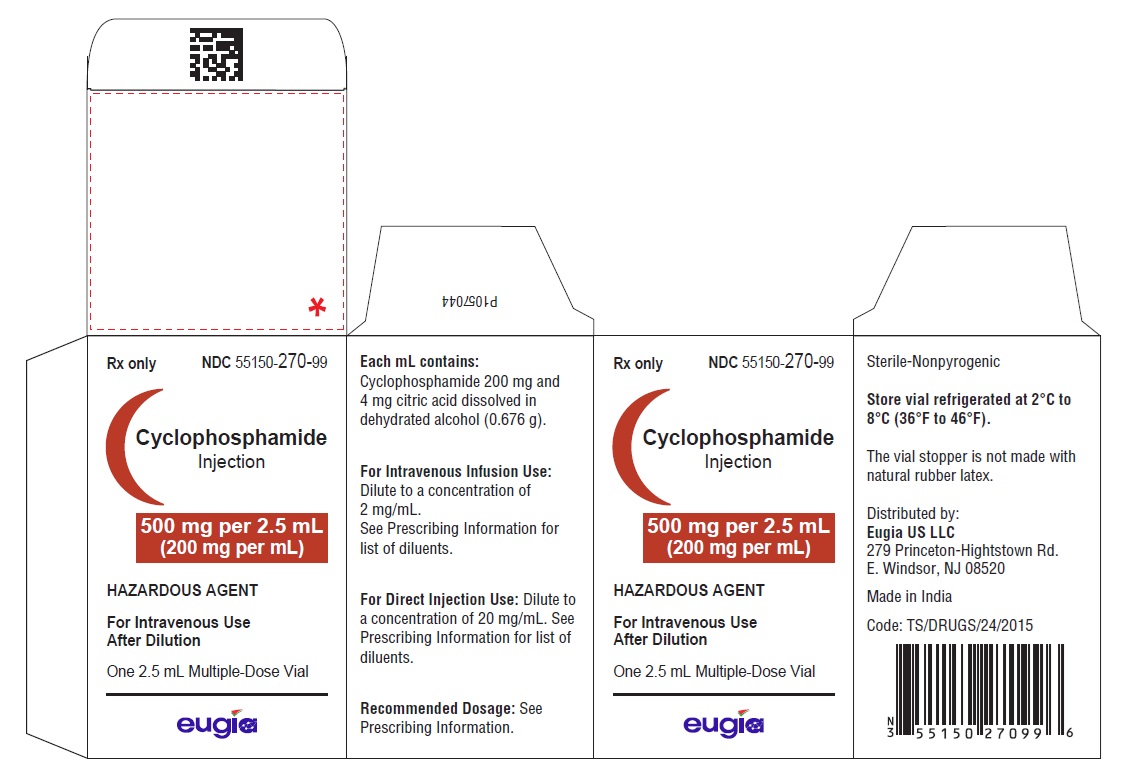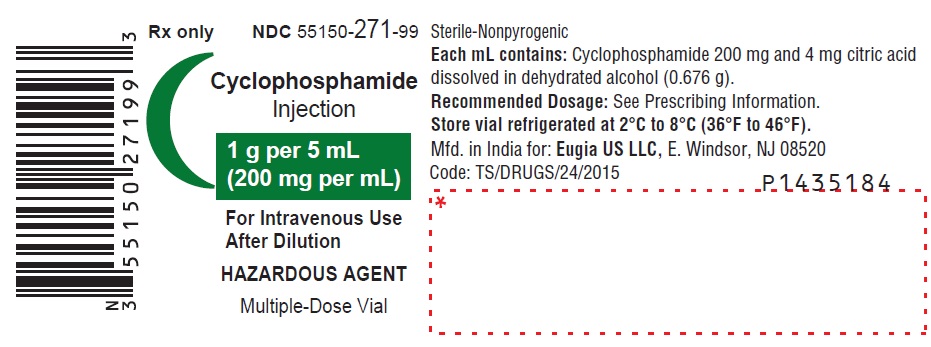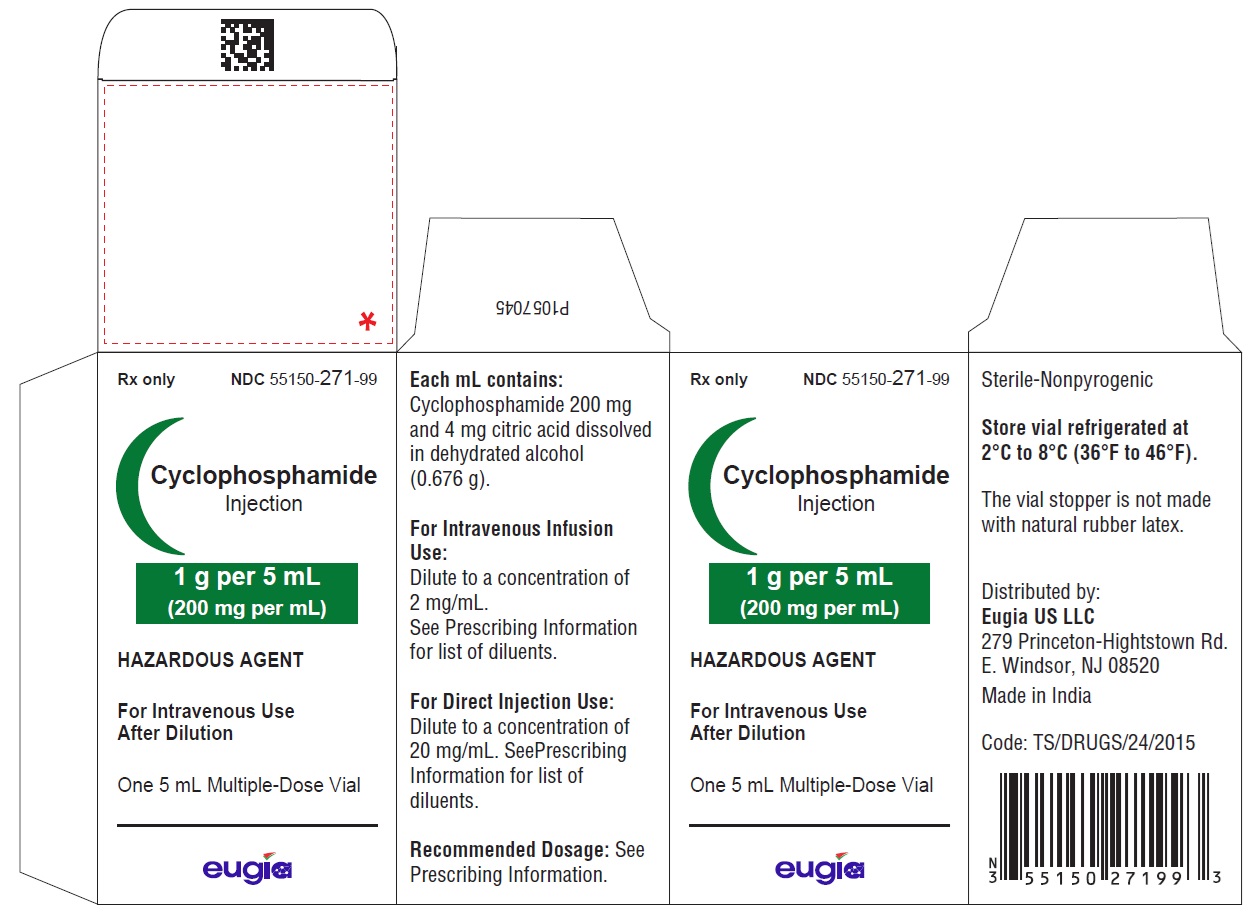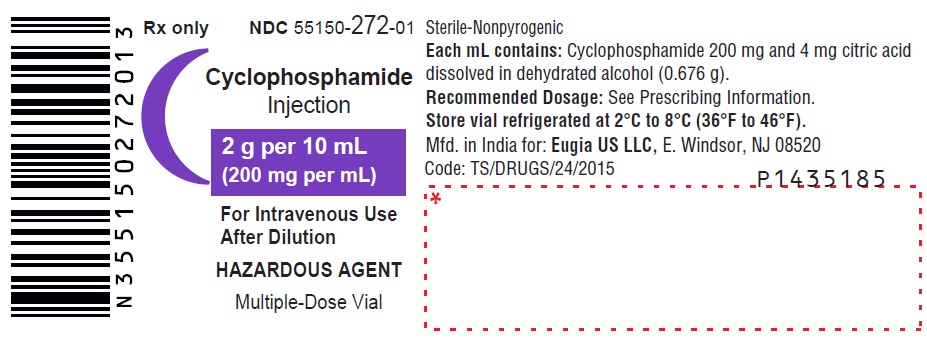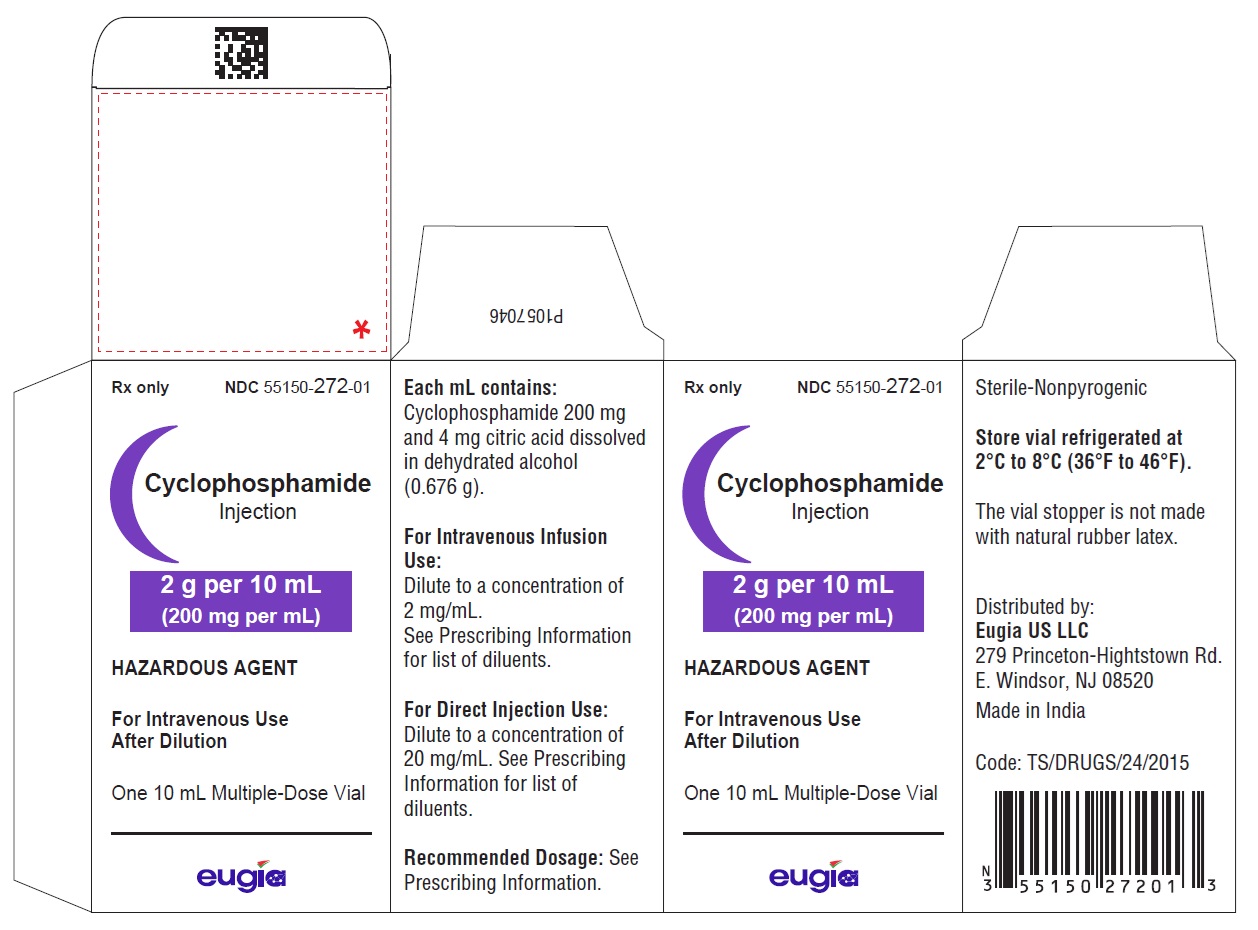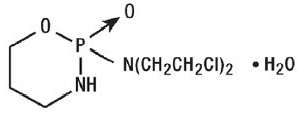 DRUG LABEL: Cyclophosphamide
NDC: 55150-270 | Form: INJECTION
Manufacturer: Eugia US LLC
Category: prescription | Type: Human Prescription Drug Label
Date: 20250421

ACTIVE INGREDIENTS: CYCLOPHOSPHAMIDE 500 mg/2.5 mL
INACTIVE INGREDIENTS: ANHYDROUS CITRIC ACID; ALCOHOL

HIGHLIGHTS OF PRESCRIBING INFORMATION

These highlights do not include all the information needed to use CYCLOPHOSPHAMIDE INJECTION safely and effectively. See full prescribing information for CYCLOPHOSPHAMIDE INJECTION.
CYCLOPHOSPHAMIDE injection, for intravenous use
Initial U.S. Approval: 1959

1 INDICATIONS AND USAGE

Cyclophosphamide Injection is an alkylating drug indicated for treatment of adult and pediatric patients with:

- Malignant Diseases: malignant lymphomas: Hodgkin’s disease, lymphocytic lymphoma, mixed-cell type lymphoma, histiocytic lymphoma, Burkitt’s lymphoma; multiple myeloma, leukemias, mycosis fungoides, neuroblastoma, adenocarcinoma of ovary, retinoblastoma, breast carcinoma (1)

2 DOSAGE AND ADMINISTRATION

Malignant Diseases: Adult and Pediatric Patients (2.1)

- Intravenous: Initial course for patients with no hematologic deficiency: 40 mg per kg to 50 mg per kg in divided doses over 2 to 5 days. Other regimens include 10 mg per kg to 15 mg per kg given every 7 to 10 days or 3 mg per kg to 5 mg per kg twice weekly. (2.2)
- See full prescribing information for instructions on preparation, handling, and administration. (2.3)

3 DOSAGE FORMS AND STRENGTHS

- Injection: 500 mg in 2.5 mL (200 mg/mL) in a multiple-dose vial (3)
- Injection: 1 g in 5 mL (200 mg/mL) in a multiple-dose vial (3)
- Injection: 2 g in 10 mL (200 mg/mL) in a multiple-dose vial (3)

4 CONTRAINDICATIONS

- Hypersensitivity to cyclophosphamide (4)
- Urinary outflow obstruction (4)

5 WARNINGS AND PRECAUTIONS

- Myelosuppression, Immunosuppression, Bone Marrow Failure and Infections – Severe immunosuppression may lead to serious and sometimes fatal infections. Close hematological monitoring is required. (5.1)
- Urinary Tract and Renal Toxicity – Hemorrhagic cystitis, pyelitis, ureteritis, and hematuria can occur. Exclude or correct any urinary tract obstructions prior to treatment. (5.2)
- Cardiotoxicity – Myocarditis, myopericarditis, pericardial effusion, arrythmias and congestive heart failure, which may be fatal, have been reported. Monitor patients, especially those with risk factors for cardiotoxicity or pre-existing cardiac disease. (5.3)
- Pulmonary Toxicity – Pneumonitis, pulmonary fibrosis and pulmonary veno-occlusive disease leading to respiratory failure may occur. Monitor patients for signs and symptoms of pulmonary toxicity. (5.4)
- Secondary malignancies (5.5)
- Veno-Occlusive Liver Disease - Fatal outcome can occur. (5.6)
- Alcohol Content - The alcohol content in a dose of Cyclophosphamide Injection may affect the central nervous system. This may include impairment of a patient’s ability to drive or use machines immediately after infusion. (5.7)
- Embryo-Fetal Toxicity - Can cause fetal harm. Advise patients of the potential risk to the fetus and to use effective contraception. (5.8, 8.1, 8.3)

6 ADVERSE REACTIONS

Common adverse reactions are neutropenia, febrile neutropenia, fever, alopecia, nausea, vomiting, and diarrhea. (6.1)

To report SUSPECTED ADVERSE REACTIONS, contact Eugia US LLC at 1-888-238-7880 or FDA at 1-800-FDA-1088 or www.fda.gov/medwatch.

8 USE IN SPECIFIC POPULATIONS

- Lactation: Advise not to breastfeed. (8.2)
- Renal Patients: Monitor for toxicity in patients with moderate and severe renal impairment. (8.6, 12.3)

FULL PRESCRIBING INFORMATION

1 INDICATIONS AND USAGE

Malignant Diseases
Cyclophosphamide Injection is indicated for the treatment of adult and pediatric patients with:

- malignant lymphomas (Stages III and IV of the Ann Arbor staging system), Hodgkin’s disease, lymphocytic lymphoma (nodular or diffuse), mixed-cell type lymphoma, histiocytic lymphoma, Burkitt’s lymphoma
- multiple myeloma
- leukemias: chronic lymphocytic leukemia, chronic granulocytic leukemia (it is usually ineffective in acute blastic crisis), acute myelogenous and monocytic leukemia, acute lymphoblastic (stem-cell) leukemia (cyclophosphamide given during remission is effective in prolonging its duration)
- mycosis fungoides (advanced disease)
- neuroblastoma (disseminated disease)
- adenocarcinoma of the ovary
- retinoblastoma
- carcinoma of the breast

Cyclophosphamide, although effective alone in susceptible malignancies, is more frequently used concurrently or sequentially with other antineoplastic drugs.

2 DOSAGE AND ADMINISTRATION

2.1 Important Dosing Information

During or immediately after the administration, adequate amounts of fluid should be ingested or infused to force diuresis in order to reduce the risk of urinary tract toxicity. Therefore, Cyclophosphamide Injection should be administered in the morning.

2.2 Recommended Dosage for Malignant Diseases

Adults and Pediatric Patients

Intravenous Use

When used as the only oncolytic drug therapy, the initial course of Cyclophosphamide Injection for patients with no hematologic deficiency usually consists of 40 mg per kg to 50 mg per kg given intravenously in divided doses over a period of 2 to 5 days. Other intravenous regimens include 10 mg per kg to 15 mg per kg given every 7 to 10 days or 3 mg per kg to 5 mg per kg twice weekly.

Dosages may also be adjusted based on antitumor activity and/or leukopenia. The total leukocyte count may be used to manage dosage.

When cyclophosphamide is included in combined cytotoxic regimens, it may be necessary to reduce the dose of Cyclophosphamide Injection as well as that of the other drugs.

2.3 Preparation, Handling, and Administration

Cyclophosphamide Injection is a hazardous drug. Follow applicable special handling and disposal procedures. ^1Caution should be exercised when handling and preparing Cyclophosphamide Injection. To minimize the risk of dermal exposure, always wear gloves when handling vials containing Cyclophosphamide Injection.
Cyclophosphamide Injection
Intravenous Administration
Parenteral drug products should be inspected visually for particulate matter and discoloration prior to administration, whenever solution and container permit. Do not use cyclophosphamide vials if there are visible particulate matter or discoloration of the solution.
Cyclophosphamide does not contain any antimicrobial preservative and thus care must be taken to assure the sterility of prepared solutions. Use aseptic technique.
For Direct Intravenous Injection
Aseptically withdraw the prescribed dose from the vial. Dilute the prescribed dose of Cyclophosphamide Injection to a concentration of 20 mg per mL by using any of the following diluents:
• 0.9% Sodium Chloride Injection, USP
• 0.45% Sodium Chloride Injection, USP
• 5% Dextrose Injection, USP
• 5% Dextrose and 0.9% Sodium Chloride Injection, USP
Do not use Sterile Water for Injection, USP because it results in a hypotonic solution and should not be injected directly.
For Intravenous Infusion
Aseptically withdraw the prescribed dose from the vial. Dilute the prescribed dose of Cyclophosphamide Injection to a concentration of 2 mg per mL by using any of the following diluents:
• 0.9% Sodium Chloride Injection, USP
• 0.45% Sodium Chloride Injection, USP
• 5% Dextrose Injection, USP
• 5% Dextrose and 0.9% Sodium Chloride Injection, USP
To reduce the likelihood of adverse reactions that appear to be administration rate-dependent (e.g., facial swelling, headache, nasal congestion, scalp burning), Cyclophosphamide Injection should be injected or infused very slowly. Duration of the infusion also should be appropriate for the volume and type of diluted solution to be infused.
Storage of Diluted Cyclophosphamide Injection Solution
If not used immediately, for microbiological integrity, Cyclophosphamide Injection solutions should be stored as described in Table 1:

Table 1: Storage of Diluted Cyclophosphamide Injection Solutions
Diluent | Storage
Diluent | Room Temperature | Refrigerated
Diluted Solutions (20 mg/mL)
0.9% Sodium Chloride Injection, USP | up to 48 hrs | up to 12 days
0.45% Sodium Chloride Injection, USP | up to 48 hrs | up to 12 days
5% Dextrose Injection, USP | up to 48 hrs | up to 12 days
5% Dextrose and 0.9% Sodium Chloride Injection, USP | up to 48 hrs | up to 12 days
Diluted Solutions (2 mg/mL)
0.9% Sodium Chloride Injection, USP | up to 48 hrs | up to 12 days
0.45% Sodium Chloride Injection, USP | up to 48 hrs | up to 12 days
5% Dextrose Injection, USP | up to 48 hrs | up to 12 days
5% Dextrose and 0.9% Sodium Chloride Injection, USP | up to 48 hrs | up to 12 days

Storage of Undiluted Cyclophosphamide Solution:
After first use, store partially used multiple-dose vial in the original carton at 2°C to 8°C (36°F to 46°F) for up to 28 days. Discard unused portion after 28 days.

3 DOSAGE FORMS AND STRENGTHS

Cyclophosphamide Injection is a sterile, colorless to slightly yellow clear solution in multiple-dose vials containing:

- 500 mg/2.5 mL (200 mg/mL)
- 1 g/5 mL (200 mg/mL)
- 2 g/10 mL (200 mg/mL)

4 CONTRAINDICATIONS

Hypersensitivity
Cyclophosphamide Injection is contraindicated in patients who have a history of severe hypersensitivity reactions to it, any of its metabolites, or to other components of the product. Anaphylactic reactions including death have been reported with cyclophosphamide. Possible cross-sensitivity with other alkylating agents can occur.

Urinary Outflow Obstruction
Cyclophosphamide Injection is contraindicated in patients with urinary outflow obstruction [see Warnings and Precautions (5.2)].

5 WARNINGS AND PRECAUTIONS

5.1 Myelosuppression, Immunosuppression, Bone Marrow Failure and Infections

Cyclophosphamide can cause myelosuppression (leukopenia, neutropenia, thrombocytopenia and anemia), bone marrow failure, and severe immunosuppression which may lead to serious and sometimes fatal infections, including sepsis and septic shock. Latent infections can be reactivated [see Adverse Reactions (6.1)].
Antimicrobial prophylaxis may be indicated in certain cases of neutropenia at the discretion of the managing healthcare provider. In case of neutropenic fever, antibiotic therapy is indicated. Antimycotics and/or antivirals may also be indicated.
Monitoring of complete blood counts is essential during cyclophosphamide treatment so that the dose can be adjusted, if needed. Cyclophosphamide Injection should not be administered to patients with neutrophils ≤1,500/mm^3 and platelets < 50,000/mm^3. Cyclophosphamide Injection treatment may not be indicated, or should be interrupted, or the dose reduced, in patients who have or who develop a serious infection. G-CSF may be administered to reduce the risks of neutropenia complications associated with cyclophosphamide use. Primary and secondary prophylaxis with G-CSF should be considered in all patients considered to be at increased risk for neutropenia complications. The nadirs of the reduction in leukocyte count and thrombocyte count are usually reached in weeks 1 and 2 of treatment. Peripheral blood cell counts are expected to normalize after approximately 20 days. Bone marrow failure has been reported. Severe myelosuppression may be expected particularly in patients pretreated with and/or receiving concomitant chemotherapy and/or radiation therapy.

5.2 Urinary Tract and Renal Toxicity

Hemorrhagic cystitis, pyelitis, ureteritis, and hematuria have been reported with cyclophosphamide. Medical and/or surgical supportive treatment may be required to treat protracted cases of severe hemorrhagic cystitis. Discontinue Cyclophosphamide Injection therapy in case of severe hemorrhagic cystitis. Urotoxicity (bladder ulceration, necrosis, fibrosis, contracture and secondary cancer) may require interruption of Cyclophosphamide Injection treatment or cystectomy. Urotoxicity can be fatal. Urotoxicity can occur with short-term or long-term use of cyclophosphamide.
Before starting treatment, exclude or correct any urinary tract obstructions [see Contraindications (4)]. Urinary sediment should be checked regularly for the presence of erythrocytes and other signs of urotoxicity and/or nephrotoxicity. Cyclophosphamide Injection should be used with caution, if at all, in patients with active urinary tract infections. Aggressive hydration with forced diuresis and frequent bladder emptying can reduce the frequency and severity of bladder toxicity. Mesna has been used to prevent severe bladder toxicity.

5.3 Cardiotoxicity

Myocarditis, myopericarditis, pericardial effusion including cardiac tamponade, and congestive heart failure, which may be fatal, have been reported with cyclophosphamide therapy
Supraventricular arrhythmias (including atrial fibrillation and flutter) and ventricular arrhythmias (including severe QT prolongation associated with ventricular tachyarrhythmia) have been reported after treatment with regimens that included cyclophosphamide.
The risk of cardiotoxicity may be increased with high doses of cyclophosphamide, in patients with advanced age, and in patients with previous radiation treatment to the cardiac region and/or previous or concomitant treatment with other cardiotoxic agents.
Particular caution is necessary in patients with risk factors for cardiotoxicity and in patients with pre-existing cardiac disease.
Monitor patients with risk factors for cardiotoxicity and with pre-existing cardiac disease.

5.4 Pulmonary Toxicity

Pneumonitis, pulmonary fibrosis, pulmonary veno-occlusive disease and other forms of pulmonary toxicity leading to respiratory failure have been reported during and following treatment with cyclophosphamide. Late onset pneumonitis (greater than 6 months after start of cyclophosphamide) appears to be associated with increased mortality. Pneumonitis may develop years after treatment with cyclophosphamide.
Monitor patients for signs and symptoms of pulmonary toxicity.

5.5 Secondary Malignancies

Cyclophosphamide is genotoxic [see Nonclinical Toxicology (13.1)]. Secondary malignancies (urinary tract cancer, myelodysplasia, acute leukemias, lymphomas, thyroid cancer, and sarcomas) have been reported in patients treated with cyclophosphamide-containing regimens.
The risk of bladder cancer may be reduced by prevention of hemorrhagic cystitis.

5.6 Veno-Occlusive Liver Disease

Veno-occlusive liver disease (VOD) including fatal outcome has been reported in patients receiving cyclophosphamide-containing regimens. A cytoreductive regimen in preparation for bone marrow transplantation that consists of cyclophosphamide in combination with whole-body irradiation, busulfan, or other agents has been identified as a major risk factor. VOD has also been reported to develop gradually in patients receiving long-term low-dose immunosuppressive doses of cyclophosphamide. Other risk factors predisposing to the development of VOD include preexisting disturbances of hepatic function, previous radiation therapy of the abdomen, and a low performance status.

5.7 Alcohol Content

The alcohol content in a dose of Cyclophosphamide Injection may affect the central nervous system and should be taken into account for patients in whom alcohol intake should be avoided or minimized. Consideration should be given to the alcohol content in Cyclophosphamide Injection on the ability to drive or use machines immediately after the infusion. Each administration of Cyclophosphamide Injection at 50 mg per kg delivers 0.17 g/kg of ethanol. For a 75 kg patient this would deliver 12.7 grams of ethanol [see Description (11)]. Other cyclophosphamide products may have a different amount of alcohol or no alcohol.

5.8 Embryo-Fetal Toxicity

Based on its mechanism of action and published reports of effects in pregnant patients or animals, Cyclophosphamide Injection can cause fetal harm when administered to a pregnant woman [see Use in Specific Populations (8.1), Clinical Pharmacology (12.1), and Nonclinical Toxicology (13.1)]. Exposure to cyclophosphamide during pregnancy may cause birth defects, miscarriage, fetal growth retardation, and fetotoxic effects in the newborn. Cyclophosphamide is teratogenic and embryo-fetal toxic in mice, rats, rabbits and monkeys.

Advise pregnant women and females of reproductive potential of the potential risk to the fetus [see Use in Specific Populations (8.1)]. Advise females of reproductive potential to use effective contraception during treatment with Cyclophosphamide Injection and for up to 1 year after completion of therapy. Advise male patients with female partners of reproductive potential to use effective contraception during treatment with Cyclophosphamide Injection and for 4 months after completion of therapy [see Use in Specific Populations (8.1, 8.3)].

5.9 Infertility

Male and female reproductive function and fertility may be impaired in patients being treated with Cyclophosphamide Injection. Cyclophosphamide interferes with oogenesis and spermatogenesis. It may cause sterility in both sexes. Development of sterility appears to depend on the dose of cyclophosphamide, duration of therapy, and the state of gonadal function at the time of treatment. Cyclophosphamide-induced sterility may be irreversible in some patients. Advise patients on the potential risks for infertility [see Use in Specific Populations (8.3, 8.4)].

5.10 Impairment of Wound Healing

Cyclophosphamide may interfere with normal wound healing.

5.11 Hyponatremia

Hyponatremia associated with increased total body water, acute water intoxication, and a syndrome resembling SIADH (syndrome of inappropriate secretion of antidiuretic hormone), which may be fatal, has been reported.

6 ADVERSE REACTIONS

The following adverse reactions are discussed in more detail in other sections of the labeling.

- Hypersensitivity [see Contraindications (4)]
- Myelosuppression, Immunosuppression, Bone Marrow Failure, and Infections [see Warnings and Precautions (5.1)]
- Urinary Tract and Renal Toxicity [see Warnings and Precautions (5.2)]
- Cardiotoxicity [see Warnings and Precautions (5.3)]
- Pulmonary Toxicity [see Warnings and Precautions (5.4)]
- Secondary Malignancies [see Warnings and Precautions (5.5)]
- Veno-Occlusive Liver Disease [see Warnings and Precautions (5.6)]
- Alcohol Content [see Warnings and Precautions (5.7)]
- Infertility [see Warnings and Precautions (5.9) and Use in Specific Populations (8.3 and 8.4)]
- Impaired Wound Healing [see Warnings and Precautions (5.10)]
- Hyponatremia [see Warnings and Precautions (5.11)]

6.1 Clinical Trials and Postmarketing Experience

The following adverse reactions associated with the use of cyclophosphamide were identified in clinical studies or postmarketing reports. Because some of these reactions were reported voluntarily from a population of uncertain size, it is not always possible to reliably estimate their frequency or establish a causal relationship to drug exposure.

The most common adverse reactions were neutropenia, febrile neutropenia, fever, alopecia, nausea, vomiting, and diarrhea.

Cardiac: cardiac arrest, ventricular fibrillation, ventricular tachycardia, cardiogenic shock, pericardial effusion (progressing to cardiac tamponade), myocardial hemorrhage, myocardial infarction, cardiac failure (including fatal outcomes), cardiomyopathy, myocarditis, pericarditis, carditis, atrial fibrillation, supraventricular arrhythmia, ventricular arrhythmia, bradycardia, tachycardia, palpitations, QT prolongation.

Congenital, Familial and Genetic: intra-uterine death, fetal malformation, fetal growth retardation, fetal toxicity (including myelosuppression, gastroenteritis).

Ear and Labyrinth: deafness, hearing impaired, tinnitus.

Endocrine: water intoxication.

Eye: visual impairment, conjunctivitis, lacrimation.

Gastrointestinal: gastrointestinal hemorrhage, acute pancreatitis, colitis, enteritis, cecitis, stomatitis, constipation, parotid gland inflammation, nausea, vomiting, diarrhea.

General Disorders and Administrative Site Conditions: multiorgan failure, general physical deterioration, influenza-like illness, injection/infusion site reactions (thrombosis, necrosis, phlebitis, inflammation, pain, swelling, erythema), pyrexia, edema, chest pain, mucosal inflammation, asthenia, pain, chills, fatigue, malaise, headache, febrile neutropenia.

Hematologic: myelosuppression, bone marrow failure, disseminated intravascular coagulation and hemolytic uremic syndrome (with thrombotic microangiopathy).

Hepatic: veno-occlusive liver disease, cholestatic hepatitis, cytolytic hepatitis, hepatitis, cholestasis; hepatotoxicity with hepatic failure, hepatic encephalopathy, ascites, hepatomegaly, blood bilirubin increased, hepatic function abnormal, hepatic enzymes increased.

Immune: immunosuppression, anaphylactic shock and hypersensitivity reaction.

Infections: The following manifestations have been associated with myelosuppression and immunosuppression caused by cyclophosphamide: increased risk for and severity of pneumonias (including fatal outcomes), other bacterial, fungal, viral, protozoal and, parasitic infections; reactivation of latent infections, (including viral hepatitis, tuberculosis), Pneumocystis jiroveci, herpes zoster, Strongyloides, sepsis and septic shock.

Investigations: blood lactate dehydrogenase increased, C-reactive protein increased.

Metabolism and Nutrition: hyponatremia, fluid retention, blood glucose increased, blood glucose decreased.

Musculoskeletal and Connective Tissue: rhabdomyolysis, scleroderma, muscle spasms, myalgia, arthralgia.

Neoplasms: acute leukemia, myelodysplastic syndrome, lymphoma, sarcomas, renal cell carcinoma, renal pelvis cancer, bladder cancer, ureteric cancer, thyroid cancer.

Nervous System: encephalopathy, convulsion, dizziness, neurotoxicity has been reported and manifested as reversible posterior leukoencephalopathy syndrome, myelopathy, peripheral neuropathy, polyneuropathy, neuralgia, dysesthesia, hypoesthesia, paresthesia, tremor, dysgeusia, hypogeusia, parosmia.

Pregnancy: premature labor.

Psychiatric: confusional state.

Renal and Urinary: renal failure, renal tubular disorder, renal impairment, nephropathy toxic, hemorrhagic cystitis, bladder necrosis, cystitis ulcerative, bladder contracture, hematuria, nephrogenic diabetes insipidus, atypical urinary bladder epithelial cells.

Reproductive System: infertility, ovarian failure, ovarian disorder, amenorrhea, oligomenorrhea, testicular atrophy, azoospermia, oligospermia.

Respiratory: pulmonary veno-occlusive disease, acute respiratory distress syndrome, interstitial lung disease as manifested by respiratory failure (including fatal outcomes), obliterative bronchiolitis, organizing pneumonia, alveolitis allergic, pneumonitis, pulmonary hemorrhage; respiratory distress, pulmonary hypertension, pulmonary edema, pleural effusion, bronchospasm, dyspnea, hypoxia, cough, nasal congestion, nasal discomfort, oropharyngeal pain, rhinorrhea.

Skin and Subcutaneous Tissue: toxic epidermal necrolysis, Stevens-Johnson syndrome, erythema multiforme, palmar-plantar erythrodysesthesia syndrome, radiation recall dermatitis, toxic skin eruption, urticaria, dermatitis, blister, pruritus, erythema, nail disorder, facial swelling, hyperhidrosis, alopecia.

Tumor lysis syndrome: like other cytotoxic drugs, cyclophosphamide may induce tumor-lysis syndrome and hyperuricemia in patients with rapidly growing tumors.

Vascular: pulmonary embolism, venous thrombosis, vasculitis, peripheral ischemia, hypertension, hypotension, flushing, hot flush.

7 DRUG INTERACTIONS

7.1 Effect of Other Drugs on Cyclophosphamide Exposure

Protease Inhibitors

Cyclophosphamide is a pro-drug that is activated by cytochrome P450s [see Clinical Pharmacology (12.3)]. Concomitant use of protease inhibitors may increase the concentration of cytotoxic metabolites. Use of protease inhibitor-based regimens was found to be associated with a higher incidence of infections and neutropenia in patients receiving cyclophosphamide, doxorubicin, and etoposide (CDE) than use of a Non-Nucleoside Reverse Transcriptase Inhibitor-based regimen.

7.2 Drugs that potentiate Cyclophosphamide Toxicities

Drugs or agents with similar toxicities to Cyclophosphamide Injection and can potentiate these effects are listed in Table 2.

Table 2: Drugs that Potentiate Cyclophosphamide Toxicities
Toxicity | Drugs
Increased hematotoxicity and/or immunosuppression | - ACE inhibitors: ACE inhibitors can cause leukopenia. - Natalizumab - Paclitaxel: Increased hematotoxicity has been reported when cyclophosphamide was administered after paclitaxel infusion. - Thiazide diuretics - Zidovudine
Increased cardiotoxicity | - Anthracyclines - Cytarabine - Pentostatin - Radiation therapy of the cardiac region - Trastuzumab
Increased pulmonary toxicity | - Amiodarone - G-CSF, GM-CSF (granulocyte colony-stimulating factor, granulocyte macrophage colony-stimulating factor)
Increased nephrotoxicity | - Amphotericin B - Indomethacin: Acute water intoxication has been reported with concomitant use of indomethacin
Increase in other toxicities: | - Azathioprine: Increased risk of hepatotoxicity (liver necrosis) - Busulfan: Increased incidence of hepatic veno-occlusive disease and mucositis has been reported. - Protease inhibitors: Increased incidence of mucositis
Increased risk of hemorrhagic cystitis | - Radiation treatment: Increased risk of hemorrhagic cystitis may result from a combined effect of cyclophosphamide and past or concomitant radiation treatment.

7.3 Effect of Cyclophosphamide on Other Drugs

Etanercept

A higher incidence of non-cutaneous malignant solid tumors in patients with Wegener’s granulomatosis occurred with the addition of etanercept to cyclophosphamide treatment.

Metronidazole

Acute encephalopathy has been reported in a patient receiving cyclophosphamide and metronidazole. In an animal study, the combination of cyclophosphamide with metronidazole was associated with increased cyclophosphamide toxicity.

Tamoxifen

Concomitant use of tamoxifen and chemotherapy may increase the risk of thromboembolic complications.

Coumarins

Both increased and decreased warfarin effect have been reported in patients receiving warfarin and cyclophosphamide.

Cyclosporine

Lower serum concentrations of cyclosporine have been observed in patients receiving a combination of cyclophosphamide and cyclosporine than in patients receiving only cyclosporine. This interaction may result in an increased incidence of graft-versus-host disease.

Depolarizing Muscle Relaxants

If a patient has been treated with cyclophosphamide within 10 days of general anesthesia, alert the anesthesiologist.

Cyclophosphamide treatment causes a marked and persistent inhibition of cholinesterase activity. Prolonged apnea may occur with concurrent depolarizing muscle relaxants (e.g., succinylcholine).

8 USE IN SPECIFIC POPULATIONS

8.1 Pregnancy

Risk Summary
Based on its mechanism of action and published reports of effects in pregnant patients or animals, Cyclophosphamide Injection can cause fetal harm when administered to a pregnant woman [see Clinical Pharmacology (12.1) and Nonclinical Toxicology (13.1)]. Exposure to cyclophosphamide during pregnancy may cause fetal malformations, miscarriage, fetal growth retardation, and toxic effects in the newborn [see Data]. Cyclophosphamide is teratogenic and embryo-fetal toxic in mice, rats, rabbits and monkeys [see Data]. Advise pregnant women and females of reproductive potential of the potential risk to the fetus.
The estimated background risk of major birth defects and miscarriage for the indicated population is unknown. In the U.S. general population, the estimated background risk of major birth defects is 2%-4% and of miscarriage is 15%-20% of clinically recognized pregnancies.
Data
Human Data
Malformations of the skeleton, palate, limbs and eyes as well as miscarriage have been reported after exposure to cyclophosphamide in the first trimester. Fetal growth retardation and toxic effects manifesting in the newborn, including leukopenia, anemia, pancytopenia, severe bone marrow hypoplasia, and gastroenteritis have been reported after exposure to cyclophosphamide.
Animal Data
Administration of cyclophosphamide to pregnant mice, rats, rabbits and monkeys during the period of organogenesis at doses at or below the dose in patients based on body surface area resulted in various malformations, which included neural tube defects, limb and digit defects and other skeletal anomalies, cleft lip and palate, and reduced skeletal ossification.

8.2 Lactation

Risk Summary
Cyclophosphamide is present in breast milk. Neutropenia, thrombocytopenia, low hemoglobin, and diarrhea have been reported in infants breast fed by women treated with cyclophosphamide. Because of the potential for serious adverse reactions in a breastfed child, advise lactating women not to breastfeed during treatment with Cyclophosphamide Injection and for 1 week after the last dose.

8.3 Females and Males of Reproductive Potential

Cyclophosphamide Injection can cause fetal harm when administered to a pregnant woman [see Use in Specific Populations (8.1)].

Pregnancy Testing
Verify the pregnancy status of females of reproductive potential prior to the initiation of Cyclophosphamide Injection [see Use in Specific Populations (8.1)].
Contraception
Females
Advise females of reproductive potential to use effective contraception during treatment with Cyclophosphamide Injection and for up to 1 year after completion of therapy [see Use in Specific Populations (8.1)].
Males
Based on findings in genetic toxicity and animal reproduction studies, advise male patients with female partners of reproductive potential to use effective contraception during treatment with Cyclophosphamide Injection and for 4 months after completion of therapy [see Use in Specific Populations (8.1) and Nonclinical Toxicology (13.1)].
Infertility
Females
Amenorrhea, transient or permanent, associated with decreased estrogen and increased gonadotropin secretion develops in a proportion of women treated with cyclophosphamide. Affected patients generally resume regular menses within a few months after cessation of therapy. The risk of premature menopause with cyclophosphamide increases with age. Oligomenorrhea has also been reported in association with cyclophosphamide treatment.
Animal data suggest an increased risk of failed pregnancy and malformations may persist after discontinuation of cyclophosphamide as long as oocytes/follicles exist that were exposed to cyclophosphamide during any of their maturation phases. The exact duration of follicular development in humans is not known but may be longer than 12 months [see Nonclinical Toxicology (13.1)].
Males
Men treated with cyclophosphamide may develop oligospermia or azoospermia which are normally associated with increased gonadotropin but normal testosterone secretion.

8.4 Pediatric Use

The safety and effectiveness of cyclophosphamide have been established in pediatric patients and information on this use is discussed throughout the labeling.

The alcohol content of Cyclophosphamide Injection should be taken into account when given to pediatric patients [see Warnings and Precautions (5.7)].

Pre-pubescent girls treated with cyclophosphamide generally develop secondary sexual characteristics normally and have regular menses. Ovarian fibrosis with apparently complete loss of germ cells after prolonged cyclophosphamide treatment in late pre-pubescence has been reported. Girls treated with cyclophosphamide who have retained ovarian function after completing treatment are at increased risk of developing premature menopause.

Pre-pubescent boys treated with cyclophosphamide develop secondary sexual characteristics normally, but may have oligospermia or azoospermia and increased gonadotropin secretion. Some degree of testicular atrophy may occur. Cyclophosphamide-induced azoospermia is reversible in some patients, though the reversibility may not occur for several years after cessation of therapy.

8.5 Geriatric Use

There is insufficient data from clinical studies of cyclophosphamide available for patients 65 years of age and older to determine whether they respond differently than younger patients. In general, dose selection for an elderly patient should be cautious, usually starting at the low end of the dosing range, reflecting the greater frequency of decreased hepatic, renal, or cardiac functioning, and of concomitant disease or other drug therapy.

8.6 Renal Impairment

In patients with severe renal impairment, decreased renal excretion may result in increased plasma levels of cyclophosphamide and its metabolites. This may result in increased toxicity [see Clinical Pharmacology (12.3)]. Monitor patients with severe renal impairment (CrCl =10 mL/min to 24 mL/min) for signs and symptoms of toxicity.
Cyclophosphamide and its metabolites are dialyzable although there are probably quantitative differences depending upon the dialysis system being used. In patients requiring dialysis, use of a consistent interval between cyclophosphamide administration and dialysis should be considered.

8.7 Hepatic Impairment

Patients with severe hepatic impairment have reduced conversion of cyclophosphamide to the active 4-hydroxyl metabolite, potentially reducing efficacy [see Clinical Pharmacology (12.3)].
The alcohol content of Cyclophosphamide Injection should be taken into account when given to patients with hepatic impairment [see Warnings and Precautions (5.7)].

10 OVERDOSAGE

No specific antidote for cyclophosphamide is known.
Overdosage should be managed with supportive measures, including appropriate treatment for any concurrent infection, myelosuppression, or cardiac toxicity should it occur.
Serious consequences of overdosage include manifestations of dose dependent toxicities such as myelosuppression, urotoxicity, cardiotoxicity (including cardiac failure), veno-occlusive hepatic disease, and stomatitis [see Warnings and Precautions (5.1, 5.2, 5.3, and 5.6)].
Patients who received an overdose should be closely monitored for the development of toxicities, and hematologic toxicity in particular.
Cyclophosphamide and its metabolites are dialyzable. Therefore, rapid hemodialysis is indicated when treating any suicidal or accidental overdose or intoxication.
Cystitis prophylaxis with mesna may be helpful in preventing or limiting urotoxic effects with cyclophosphamide overdose.

11 DESCRIPTION

Cyclophosphamide is an alkylating drug. It is an antineoplastic drug chemically related to the nitrogen mustards. The chemical name for cyclophosphamide is 2-[bis(2-chloroethyl)amino]tetrahydro-2H-1,3,2-oxazaphosphorine 2-oxide monohydrate, and has the following structural formula:

Cyclophosphamide has a molecular formula of C7H15Cl2N2O2P•H2O and a molecular weight of 279.1. Cyclophosphamide is soluble in water, saline, or ethanol.
Cyclophosphamide Injection is a sterile, colorless to slightly yellow clear solution available in clear glass vials for multiple-dose use. Vials of Cyclophosphamide Injection are available in three presentations:

- 500 mg per 2.5 mL vial contains 500 mg anhydrous cyclophosphamide (equivalent to 534 mg cyclophosphamide monohydrate) and 10 mg citric acid dissolved in dehydrated alcohol (1.69 grams).
- 1 g per 5 mL vial contains 1 gram anhydrous cyclophosphamide (equivalent to 1.07 g cyclophosphamide monohydrate) and 20 mg citric acid dissolved in dehydrated alcohol (3.38 grams).
- 2 g per 10 mL vial contains 2 gram anhydrous cyclophosphamide (equivalent to 2.14 g cyclophosphamide monohydrate) and 40 mg citric acid dissolved in dehydrated alcohol (6.76 grams).

12 CLINICAL PHARMACOLOGY

12.1 Mechanism of Action

The mechanism of action has not been fully characterized. However, cross-linking of tumor cell DNA may be involved.

The active alkylating metabolites of cyclophosphamide interfere with the growth of susceptible rapidly proliferating malignant cells.

12.2 Pharmacodynamics

Cyclophosphamide exposure-response relationships and the time course of pharmacodynamic response have not been fully characterized.

12.3 Pharmacokinetics

Cyclophosphamide is a prodrug. Cyclophosphamide pharmacokinetics are linear over the approved recommended dose range.

Distribution

Cyclophosphamide volume of distribution approximates total body water (30 to 50 L). Cyclophosphamide is approximately 20% protein bound, with no dose dependent changes. Some metabolites are greater than 60% protein bound.

Elimination

The cyclophosphamide elimination half-life ranges from 3 to 12 hours with total body clearance (CL) values of 4 to 5.6 L/h following IV administration. Cyclophosphamide appears to induce its own metabolism. This auto-induction results in an increase in the total clearance, increased formation of active 4-hydroxyl metabolites and shortened elimination half-life values following repeated administration at 12- to 24-hour interval.

Cyclophosphamide and its metabolites are eliminated by both a hepatic pathway and a renal pathway. When cyclophosphamide was administered at 4.0 g/m2 (approximately 2 times the approved recommended dosage) over a 90-minutes infusion, saturable elimination in parallel with first-order renal elimination describe the kinetics of the drug.

Metabolism

The liver is the major site of cyclophosphamide activation. Approximately 75% of the administered dose of cyclophosphamide is activated by hepatic microsomal cytochrome P450s including CYP2A6, 2B6, 3A4, 3A5, 2C9, 2C18 and 2C19, with 2B6 displaying the highest 4-hydroxylase activity. Cyclophosphamide is activated to form 4-hydroxycyclophosphamide, which is in equilibrium with its ring-open tautomer aldophosphamide. 4-hydroxycyclophosphamide and aldophosphamide can undergo oxidation by aldehyde dehydrogenases to form the inactive metabolites 4-ketocyclophosphamide and carboxyphosphamide, respectively. Aldophosphamide can undergo β-elimination to form active metabolites phosphoramide mustard and acrolein. This spontaneous conversion can be catalyzed by albumin and other proteins. Less than 5% of cyclophosphamide may be directly detoxified by side chain oxidation, leading to the formation of inactive metabolites 2-dechloroethylcyclophosphamide. At high doses, the fraction of parent compound cleared by 4-hydroxylation is reduced resulting in non-linear elimination of cyclophosphamide in patients.

Excretion

Cyclophosphamide is primarily excreted as metabolites. 10 to 20% is excreted unchanged in the urine and 4% is excreted in the bile following IV administration.

Specific Populations

Renal Impairment

Cyclophosphamide exposure increased following one-hour intravenous infusion to renally impaired patients. Mean dose-corrected cyclophosphamide AUC increased by 38% in the moderate renal group, (Creatinine clearance (CrCl of 25 to 50 mL/min), by 64% in the severe renal group (CrCl of 10 to 24 mL/min) and by 23% in the hemodialysis group (CrCl of < 10mL/min) compared to the control group.

Cyclophosphamide is dialyzable. Dialysis clearance averaged 104 mL/min (calculated by arterial-venous difference and actual drug recovery in dialysate), which is in the range of the metabolic clearance of 95 mL/min for the drug. A mean of 37% of the administered dose of cyclophosphamide was removed during hemodialysis. The elimination half-life (t1/2) was 3.3 hours in patients during hemodialysis, a 49% reduction of the 6.5 hours to t1/2 was reported in uremic patients.

Hepatic Impairment

Cyclophosphamide total body clearance (CL) is decreased by 40% in patients with severe hepatic impairment and elimination half-life (t½) is prolonged by 64%. Mean CL and t½ were 45 ± 8.6 L/kg and 12.5 ± 1.0 hours respectively, in patients with severe hepatic impairment.

13 NONCLINICAL TOXICOLOGY

13.1 Carcinogenesis, Mutagenesis, Impairment of Fertility

Cyclophosphamide administered by different routes, including intravenous, subcutaneous or intraperitoneal injection, or in drinking water, caused tumors in both mice and rats. In addition to leukemia and lymphoma, benign and malignant tumors were found at various tissue sites, including urinary bladder, mammary gland, lung, liver, and injection site [see Warnings and Precautions (5.5)].
Cyclophosphamide was mutagenic and clastogenic in multiple in vitro and in vivo genetic toxicology studies.
Cyclophosphamide is genotoxic in male and female germ cells. Animal data indicate that exposure of oocytes to cyclophosphamide during follicular development may result in a decreased rate of implantations and viable pregnancies, and in an increased risk of malformations. Male mice and rats treated with cyclophosphamide show alterations in male reproductive organs (e.g., decreased weights, atrophy, changes in spermatogenesis), and decreases in reproductive potential (e.g., decreased implantations and increased post-implantation loss) and increases in fetal malformations when mated with untreated females [see Use in Specific Populations (8.3)].

15 REFERENCES

1. “OSHA Hazardous Drugs.” OSHA. http://www.osha.gov/SLTC/hazardousdrugs/index.html

16 HOW SUPPLIED/STORAGE AND HANDLING

Cyclophosphamide Injection is a colorless to slightly yellow clear solution supplied in multiple-dose vial.
Cyclophosphamide Injection:
NDC 55150-270-99 500 mg/2.5 mL (200 mg/mL), carton of 1 vial

NDC 55150-271-99 1 g/5 mL (200 mg/mL), carton of 1 vial

NDC 55150-272-01 2 g/10 mL (200 mg/mL), carton of 1 vial
Storage:
Store vials refrigerated at 2°C to 8°C (36°F to 46°F).
Cyclophosphamide is a hazardous drug. Follow special handling and disposal procedures.^1
The vial stopper is not made with natural rubber latex.

17 PATIENT COUNSELING INFORMATION

Advise the patient of the following:
Myelosuppression, Immunosuppression, Bone Marrow Failure, and Infections

- Inform patients of the possibility of myelosuppression, immunosuppression, bone marrow failure, and infections. Explain the need for routine blood cell counts. Instruct patients to monitor their temperature frequently and immediately report any occurrence of fever [see Warnings and Precautions (5.1)].

Urinary Tract and Renal Toxicity

- Advise the patient to report urinary symptoms (patients should report if their urine has turned a pink or red color) and the need for increasing fluid intake and frequent voiding [see Warnings and Precautions (5.2)].

Cardiotoxicity

- Advise patients to contact a health care professional immediately for any of the following: new onset or worsening shortness of breath, cough, swelling of the ankles/legs, palpitations, weight gain of more than 5 pounds in 24 hours, dizziness or loss of consciousness [see Warnings and Precautions (5.3)].

Pulmonary Toxicity

- Warn patients of the possibility of developing non-infectious pneumonitis. Advise patients to report promptly any new or worsening respiratory symptoms [see Warnings and Precautions (5.4)].

Alcohol Content

- Explain to patients the possible effects of the alcohol content in Cyclophosphamide Injection, including possible effects on the central nervous system. Patients in whom alcohol should be avoided or minimized should consider the alcohol content of Cyclophosphamide Injection. Alcohol could impair their ability to drive or use machines immediately after infusion [see Warnings and Precautions (5.7)].

Embryo-Fetal Toxicity

- Inform female patients of the risk to a fetus and potential loss of the pregnancy. Advise females to inform their healthcare provider of a known or suspected pregnancy [see Warnings and Precautions (5.8) and Use in Specific Populations (8.1)].
- Advise females of reproductive potential to use effective contraception during treatment and for up to 1 year after completion of therapy [See Warning and Precautions (5.8) and Use in Specific Population (8.1, 8.3)]. Advise male patients with female partners of reproductive potential to use effective contraception during treatment and for 4 months after completion of therapy [see Warnings and Precautions (5.8) and Use in Specific Populations (8.1, 8.3)].

Lactation

- Advise lactating women not to breastfeed during treatment and for 1 week after the last dose of Cyclophosphamide Injection [see Use in Specific Populations (8.2)].

Infertility

- Advise males and females of reproductive potential that Cyclophosphamide Injection may impair fertility [see Warnings and Precautions (5.9) and Use in Specific Populations (8.3, 8.4)].

Common Adverse Reactions

- Explain to patients that side effects such as nausea, vomiting, stomatitis, impaired wound healing, amenorrhea, premature menopause, sterility and hair loss may be associated with cyclophosphamide administration. Other undesirable effects (including, e.g., dizziness, blurred vision, visual impairment) could affect the ability to drive or use machines [see Adverse Reactions (6)].

Distributed by:
Eugia US LLC
279 Princeton-Hightstown Rd.
E. Windsor, NJ 08520

Manufactured by:
Eugia Pharma Specialities Limited
Hyderabad - 500032
India

PACKAGE LABEL-PRINCIPAL DISPLAY PANEL- 500 mg per 2.5 mL (200 mg per mL) - Container Label

Rx only NDC 55150-270-99
Cyclophosphamide
Injection
500 mg per 2.5 mL
(200 mg per mL)
For Intravenous Use After Dilution

HAZARDOUS AGENT Multiple-Dose Vial

PACKAGE LABEL-PRINCIPAL DISPLAY PANEL-500 mg per 2.5 mL (200 mg per mL) - Container-Carton (1 Vial)

Rx only NDC 55150-270-99
Cyclophosphamide
Injection
500 mg per 2.5 mL
(200 mg per mL)
HAZARDOUS AGENT
For Intravenous Use
After Dilution
One 2.5 mL Multiple-Dose Vial
eugia

PACKAGE LABEL-PRINCIPAL DISPLAY PANEL- 1 g per 5 mL (200 mg per mL) - Container Label

Rx only NDC 55150-271-99
Cyclophosphamide
Injection
1 g per 5 mL
(200 mg per mL)
For Intravenous Use
After Dilution
HAZARDOUS AGENT
Multiple-Dose Vial

PACKAGE LABEL-PRINCIPAL DISPLAY PANEL-1 g per 5 mL (200 mg per mL) - Container-Carton (1 Vial)

Rx only NDC 55150-271-99
Cyclophosphamide
Injection
1 g per 5 mL
(200 mg per mL)
HAZARDOUS AGENT
For Intravenous Use
After Dilution
One 5 mL Multiple-Dose Vial
eugia

PACKAGE LABEL-PRINCIPAL DISPLAY PANEL-2 g per 10 mL (200 mg per mL) - Container Label

Rx only NDC 55150-272-01
Cyclophosphamide
Injection
2 g per 10 mL
(200 mg per mL)
For Intravenous Use
After Dilution
HAZARDOUS AGENT
Multiple-Dose Vial

PACKAGE LABEL-PRINCIPAL DISPLAY PANEL-2 g per 10 mL (200 mg per mL) - Container-Carton (1 Vial)

Rx only NDC 55150-272-01
Cyclophosphamide
Injection
2 g per 10 mL
(200 mg per mL)
HAZARDOUS AGENT
For Intravenous Use
After Dilution
One 10 mL Multiple-Dose Vial
eugia